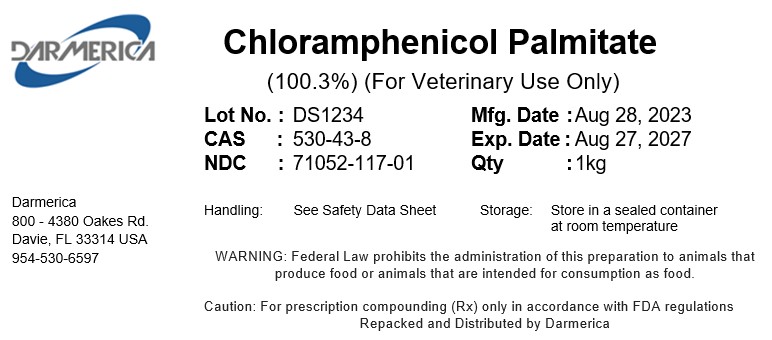 DRUG LABEL: Chloramphenicol Palmitate
NDC: 71052-117 | Form: POWDER
Manufacturer: DARMERICA, LLC
Category: other | Type: BULK INGREDIENT - ANIMAL DRUG
Date: 20241219

ACTIVE INGREDIENTS: CHLORAMPHENICOL PALMITATE 1 kg/1 kg

Chloramphenicol Palmitate